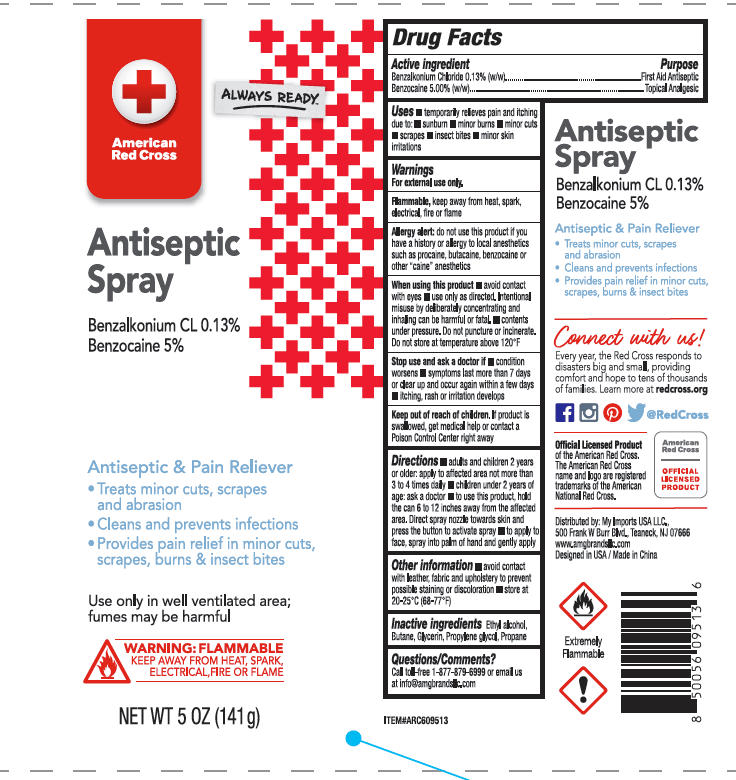 DRUG LABEL: American Red Cross Antiseptic
NDC: 51628-4528 | Form: SPRAY
Manufacturer: MY IMPORTS USA LLC
Category: otc | Type: HUMAN OTC DRUG LABEL
Date: 20251027

ACTIVE INGREDIENTS: BENZOCAINE 5 g/100 g; BENZALKONIUM CHLORIDE 0.13 g/100 g
INACTIVE INGREDIENTS: GLYCERIN; PROPANE; BUTANE; ALCOHOL; PROPYLENE GLYCOL

American Red Cross Antiseptic Spray

Active ingredient

Benzalkonium Chloride 0.13%(w/w)

Benzocaine 5.00%(w/w)

Purpose

First Aid Antiseptic

Topical Analgesic

Uses

- temporarily relieves pain and itching due to: subburn, minor burns, minor cuts, scrapes, insect bite, minor skin irritations

Warnings

For external use only.

Flammable, keep away from heat, spark, electrical, fire or flame.

Do not use

Allergy alert: do not use this product if you have a history or allergy to local anesthetics such as procaine, butacaine, benzocaine or other "caine" anesthetics.

When using this product

- avoid contact with eyes
- use only as directed. Intentional misuse by deliberately concentrating and inhaling can be harmful or fatal.
- contents under pressure. Do not puncture or incinerate. Do not store at temperature above 120ºF.

Stop use and ask a doctor if

- condition worsens
- symptoms last more than 7 days or clear up and occur again with a few days
- itching, rash or irritation develops

Keep out of reach of children

If product is swallowed, get medical help or contact a Poison Control Center right away.

Directions

- adult and children 2 years or older: apply to affected area not more than 3 to 4 times daily.
- children under 2 years of age: ask a doctor
- to use this product, hold the can 6 to 12 inches away from the affected area. Direct apray nozzles towards skin and press the button to activate spray
- to apply to face, spray into palm of hand and gently apply.

Other information

- avoid contact with leather, fabric and upholstery to prevent possible staining or discoloration
- store at 20-25 ºC (68-77ºF)

Inactive ingredients

Propane

Ethyl alcohol

Butane

Glycerin

Propylene glycol